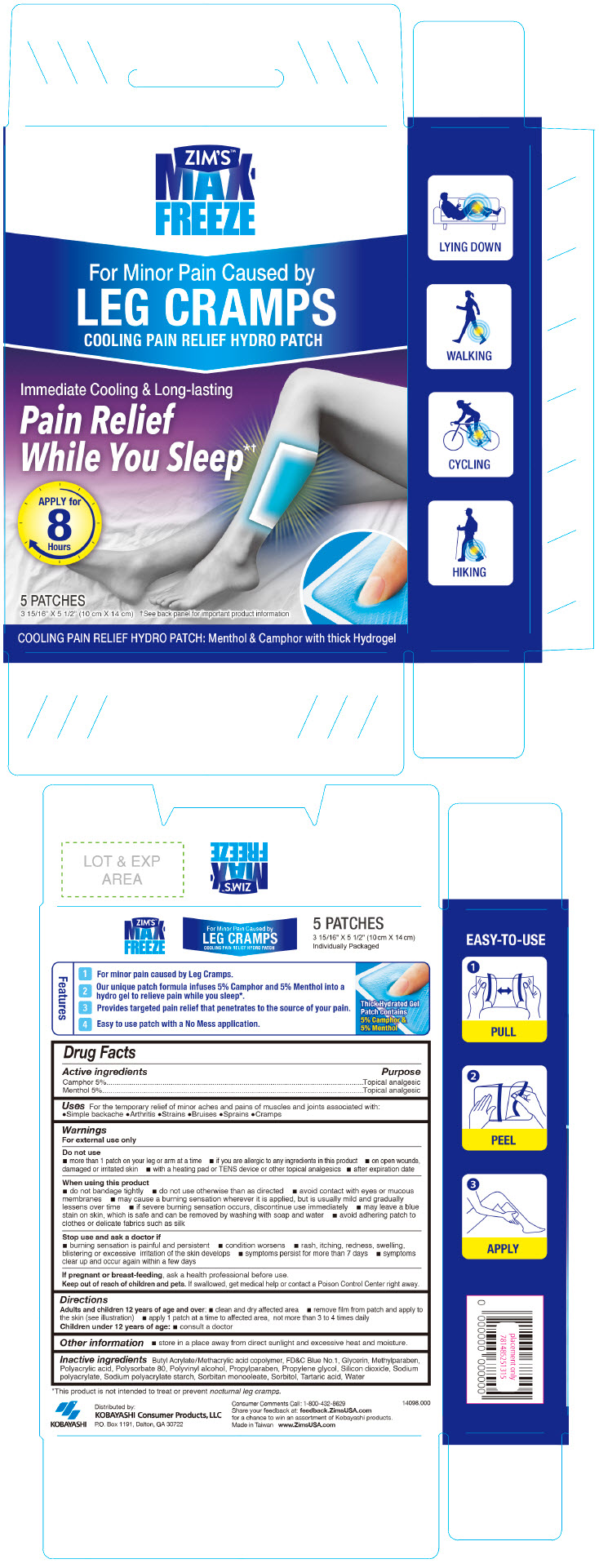 DRUG LABEL: ZIMS MAX FREEZE 
NDC: 54273-013 | Form: PATCH
Manufacturer: KOBAYASHI Healthcare International, Inc.
Category: otc | Type: HUMAN OTC DRUG LABEL
Date: 20240118

ACTIVE INGREDIENTS: CAMPHOR (SYNTHETIC) 950 mg/1 1; MENTHOL, UNSPECIFIED FORM 950 mg/1 1
INACTIVE INGREDIENTS: BUTYL ACRYLATE/METHACRYLIC ACID COPOLYMER (2% METHACRYLIC ACID); FD&C BLUE NO. 1; GLYCERIN; METHYLPARABEN; POLYACRYLIC ACID (300000 MW); POLYSORBATE 80; POLYVINYL ALCOHOL, UNSPECIFIED; PROPYLENE GLYCOL; PROPYLPARABEN; SODIUM POLYACRYLATE (2500000 MW); SODIUM POLYACRYLATE STARCH (25 MICROMETER PARTICLE); SORBITAN MONOOLEATE; SORBITOL; TARTARIC ACID; SILICON DIOXIDE; WATER

ZIM'S™ MAX-FREEZE
LEG CRAMPS

Drug Facts

ACTIVE INGREDIENT

Active ingredients | Purpose
Camphor 5% | Topical analgesic
Menthol 5% | Topical analgesic

Uses

For the temporary relief of minor aches and pains of muscles and joints associated with:

- Simple backache
- Arthritis
- Strains
- Bruises
- Sprains
- Cramps

Warnings

For external use only

Do not use

- more than 1 patch on your leg or arm at a time
- if you are allergic to any ingredients in this product
- on open wounds, damaged or irritated skin
- with a heating pad or TENS device or other topical analgesics
- after expiration date

When using this product

- do not bandage tightly
- do not use otherwise than as directed
- avoid contact with eyes or mucous membranes
- may cause a burning sensation wherever it is applied, but is usually mild and gradually lessens over time
- if severe burning sensation occurs, discontinue use immediately
- may leave a blue stain on skin, which is safe and can be removed by washing with soap and water
- avoid adhering patch to clothes or delicate fabrics such as silk

Stop use and ask a doctor if

- burning sensation is painful and persistent
- condition worsens
- rash, itching, redness, swelling, blistering or excessive irritation of the skin develops
- symptoms persist for more than 7 days
- symptoms clear up and occur again within a few days

PREGNANCY OR BREAST FEEDING

If pregnant or breast-feeding, ask a health professional before use.

Keep out of reach of children and pets. If swallowed, get medical help or contact a Poison Control Center right away.

Directions

Adults and children 12 years of age and over:

- clean and dry affected area
- remove film from patch and apply to the skin (see illustration)
- apply 1 patch at a time to affected area, not more than 3 to 4 times daily

Children under 12 years of age:

- consult a doctor

Other information

- store in a place away from direct sunlight and excessive heat and moisture.

Inactive ingredients

Butyl Acrylate/Methacrylic acid copolymer, FD&C Blue No. 1, Glycerin, Methylparaben, Polyacrylic acid, Polysorbate 80, Polyvinyl alcohol, Propylparaben, Propylene glycol, Silicon dioxide, Sodium polyacrylate, Sodium polyacrylate starch, Sorbitan monooleate, Sorbitol, Tartaric acid, Water

Distributed by:
KOBAYASHI Consumer Products, LLC
P.O. Box 1191, Dalton, GA 30722

PRINCIPAL DISPLAY PANEL - 5 Patch Pouch Box

ZIM'S™
MAX-
FREEZE

For Minor Pain Caused by
LEG CRAMPS
COOLING PAIN RELIEF HYDRO PATCH

Immediate Cooling & Long-lasting
Pain Relief
While You Sleep*†

APPLY for
8
Hours

5 PATCHES

3 15/16" X 5 1/2" (10 cm X 14 cm)
†See back panel for important product information

COOLING PAIN RELIEF HYDRO PATCH: Menthol & Camphor with thick Hydrogel